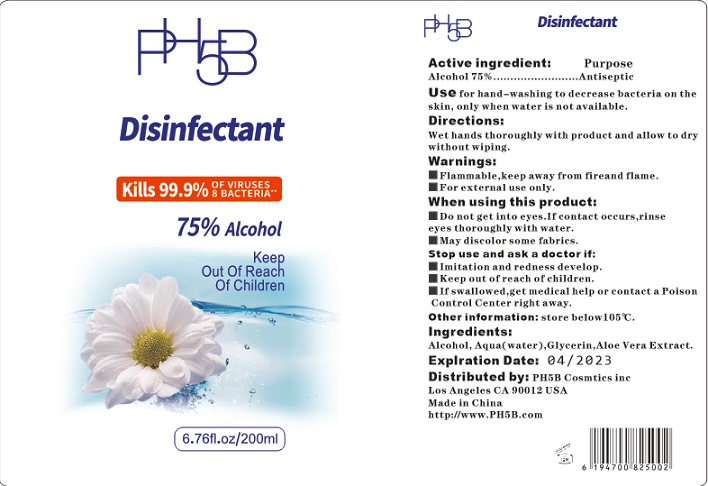 DRUG LABEL: PH5B Disinfectant
NDC: 76718-006 | Form: SOLUTION
Manufacturer: Guangzhou Jukang Sanitary Products Co., Ltd.
Category: otc | Type: HUMAN OTC DRUG LABEL
Date: 20200425

ACTIVE INGREDIENTS: ALCOHOL 75 mL/100 mL
INACTIVE INGREDIENTS: WATER; GLYCERIN; PROPYLENE GLYCOL; SODIUM HYDROXIDE

Active ingredient

Ethyl Alcohol 75%

Purpose

Antiseptic

Use

For hand-washing to decrease bacteria on the skin, only when water is not available.

KEEP OUT OF REACH OF CHILDREN

if swallowed, get medical help or contact a Poison Control Center right away.

Children must be supervised in use of this product.

warnings:

Flamable, keep away from fire and flames

For external use only

Do not get into eyes, if contact occurs, rinse eyes thoroughly with water.

When using this product, avoid contact with eyes. In case of contact, flush eyes with water.

Stop use and ask a doctor if irritation and redness develop.

Directions

- wet hands thoroughl with product and allow to dry without wiping.

Inactive ingredients

Aqua (water), Glycerin, aloe vera Extract.